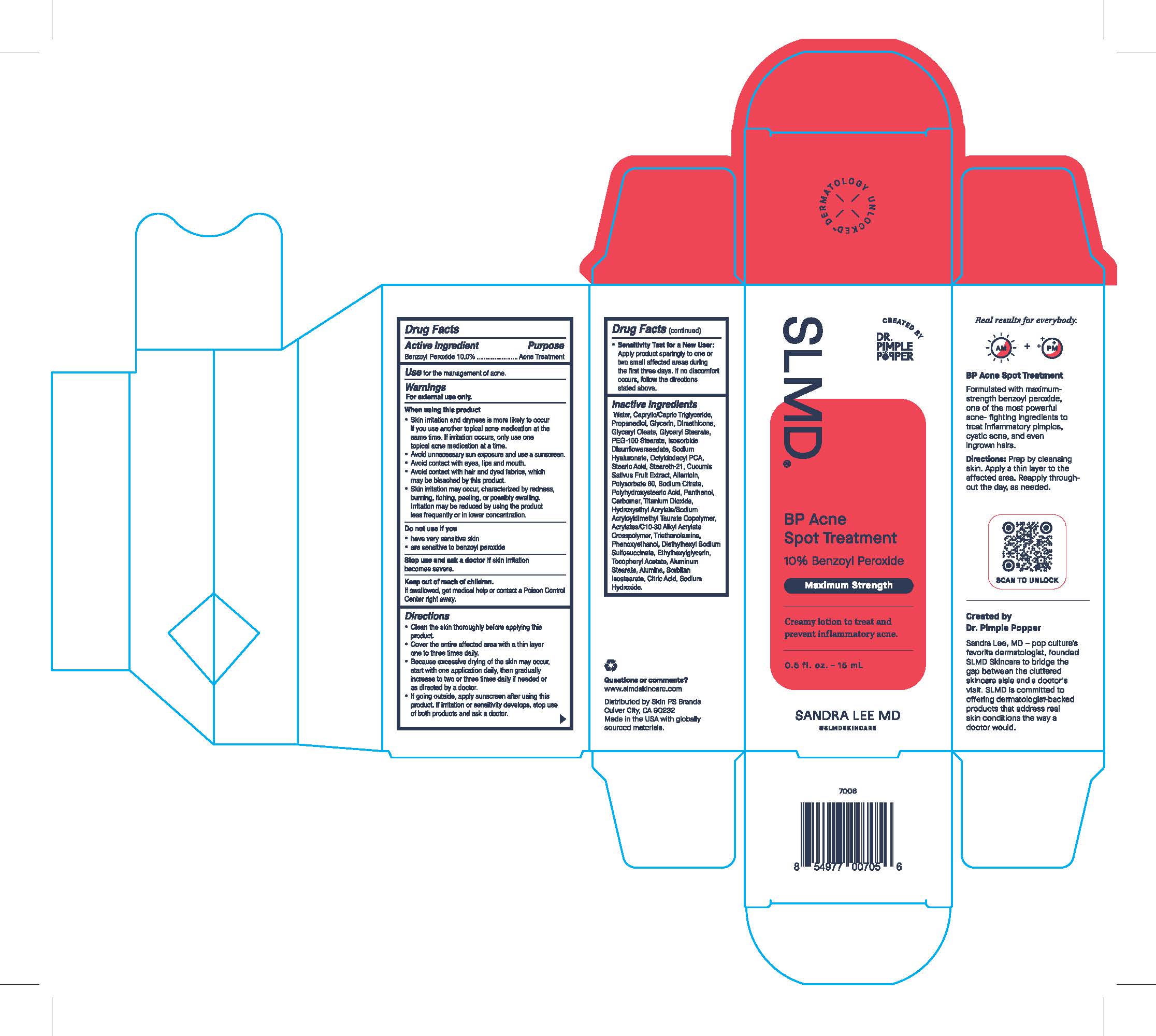 DRUG LABEL: BP Acne Spot Treatment
NDC: 73318-7002 | Form: LOTION
Manufacturer: Skin PS Brands
Category: otc | Type: HUMAN OTC DRUG LABEL
Date: 20251230

ACTIVE INGREDIENTS: BENZOYL PEROXIDE 100 mg/1 g
INACTIVE INGREDIENTS: MEDIUM-CHAIN TRIGLYCERIDES; PROPANEDIOL; TROLAMINE; POLYSORBATE 60; GLYCERIN; GLYCERYL OLEATE; GLYCERYL STEARATE SE; PEG-100 STEARATE; WATER; HYALURONATE SODIUM; 2-OCTYLDODECYL 5-OXO-L-PROLINATE; STEARIC ACID; STEARETH-21; CUCUMBER; CARBOMER HOMOPOLYMER, UNSPECIFIED TYPE; TITANIUM DIOXIDE; ETHYLHEXYLGLYCERIN; ALUMINUM OXIDE; CITRIC ACID MONOHYDRATE; SODIUM HYDROXIDE; SORBITAN ISOSTEARATE; POLYHYDROXYSTEARIC ACID (2300 MW); PANTHENOL; HYDROXYETHYL ACRYLATE/SODIUM ACRYLOYLDIMETHYL TAURATE COPOLYMER (45000 MPA.S AT 1%); PHENOXYETHANOL; .ALPHA.-TOCOPHEROL ACETATE; SODIUM CITRATE; DOCUSATE SODIUM; ALUMINUM STEARATE; CARBOMER INTERPOLYMER TYPE A (55000 CPS); DIMETHICONE; ALLANTOIN

BP Acne Spot Treatment

Active Ingredient

Benzoyl Peroxide 10.0%

Purpose

Acne Treatment

Use

for the management of acne.

Warnings

For external use only.

When using this product

- Skin irritation and dryness is more likely to occur if you use another topical acne medication at the same time. If irritation occurs, only use one topical acne medication at a time.
- avoid unnecessary sun exposure and use a sunscreen.
- avoid contact with eyes, lips and mouth.
- avoid contact with hair and dyed fabrics, which may be bleached by this product.
- Skin irritation may occur, characterized by redness, burning, itching, peeling, or possibly swelling. Irritation may be reduced by using the product less frequently or in a lower concentration.

Do not use if you

- have very sensitive skin
- are sensitive to Benzoyl Peroxide

Stop use and ask a doctor if

irritation becomes severe.

Keep out of reach of children.

If swallowed, get medical help or contact a Poison Control Center right away.

Directions

- Clean the skin thoroughly before applying this product.
- Cover the entire affected area with a thin layer one to three times daily.
- Because excessive drying of the skin may occur, start with one application daily, then gradually increase to two or three daily if needed or as directed by a doctor.
- If going outside, apply sunscreen after using this product. If irritation or sensitivity develops, stop use of both products and ask a doctor.
- Sensitivity Test for a New User:
- Apply product sparingly to one or two small affected areas during the first three days. if no discomfort occurs, follow the directions stated above.

Inactive Ingredients

Water, Caprylic/Capric Triglyceride, Propanediol, Glycerin, Dimethicone, Glyceryl Oleate, Glyceryl Stearate, PEG-100 Stearate, Isosorbide Disunflowerseedate, Sodium Hyaluronate, Octyldodecyl PCA, Stearic Acid, Steareth-21, Cucumis Sativus Fruit Extract, Allantoin, Polysorbate 60, Sodium Citrate, Polyhydroxystearic Acid, Panethol, Carbomer, Titanium Dioxide, Hydroxyethyl Acrylate/Sodium Acryloyldimethyl Taurate Copolymer, Acrylates/C10-30 Alkyl Acrylate Crosspolymer, Triethanolamine, Phenoxyethanol, Diethylhexyl Sodium Sulfosuccinate, Ethylhexylglycerin, Tocopheryl Acetate, Aluminum Stearate, Alumina, Sorbitan Isostearate, Citric Acid, Sodium Hydroxide.

Questions or comments?

www.slmdskincare.com

Distributed by Skin PS Brands

Culver City, CA 90232

Made in the USA with globally sourced materials.

SLMD Sandra Lee MD

Skin Care by Dr. Pimple Popper

BP Acne Spot Treatment

10% Benzoyl Peroxide

Maximum Strength

Creamy lotion to treat and prevent inflammatory acne.

0.5 fl. oz. - 15 mL

SANDRA LEE MD

@SLMDSKINCARE

Unit Carton:

Real results for everybody.

AM + PM

BP Acne Spot Treatment

Formulated with maximum-strength benzoyl peroxide, one of the mose powerful acne-fighting ingredients to treat inflammatory pimples, cystic acne, and even ingrown hairs.

Directions: Prep by cleansing skin. Apply a thin layer to the affected area. Reapply throughout the day, as needed.

Created by Dr. Pimple Popper

Sandra Lee, MD - pop culture's favorite dermatologist, founded SLMD Skincare to bridge the gap between the cluttered skincare aisle and a doctor's visit. SLMD is committed to offering dermatologist-backed products that address real skin conditions the way a doctor would.